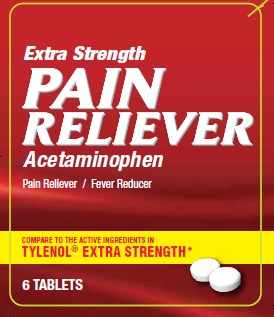 DRUG LABEL: EXTRA STRENGTH PAIN RELIEVER
NDC: 29485-7626 | Form: TABLET
Manufacturer: Mechanical Servants LLC
Category: otc | Type: HUMAN OTC DRUG LABEL
Date: 20211006

ACTIVE INGREDIENTS: ACETAMINOPHEN 500 1/1 1
INACTIVE INGREDIENTS: STARCH, CORN; CELLULOSE, MICROCRYSTALLINE; POVIDONE; SODIUM STARCH GLYCOLATE TYPE A POTATO; STEARIC ACID; HYPROMELLOSE, UNSPECIFIED; MALTODEXTRIN; POLYETHYLENE GLYCOL 400

ACTIVE INGREDIENT IN EACH TABLET-

Acetaminophen 500 mg

PURPOSE

Analgesic, Antipyretic (fever reducer)

INDICATIONS AND USAGE

Uses: temporarily relieves minor aches and pains due to: • headache • common cold • toothache • backache • muscular aches • menstrual cramps • minor arthritis pain

Temporarily reduces fever

Warnings:

Liver Warning: This product contains acetaminophen. Severe liver damage may occur if you take: • more than 8 tablets in 24 hours, which is the maximum daily amount • with other drugs containing acetaminophen (prescription or non-prescription). Ask a doctor or pharmacist before using with other drugs if you are not sure. • you have 3 or more alcoholic drinks every day while using this product

Allergy alert: acetaminophen may cause severe skin reactions. Symptoms may include:

• skin reddening

• blisters

• rash

If a skin reaction occurs, stop use and seek medical help right away.

Do not use: • with any other product containing acetaminophen this will provide more than the recommended dose (overdose) of acetaminophen and could cause serious health concerns.

When using this product do not exceed recommended dose.

Ask a doctor before use if you have liver disease

Ask a doctor or pharmacist before use if you are taking the blood thinning drug warfarin

Stop use and ask a doctor if: • pain or fever persists or gets worse or lasts for more than 10 days • fever gets worse or lasts for more than 3 days • new symptoms occur • redness or swelling is present. These could be signs of a serious condition.

PREGNANCY OR BREAST FEEDING

If pregnant or breast-feeding, ask a health professional before use.

KEEP OUT OF REACH OF CHILDREN. In case of overdose, get medical help or contact a Poison Control Center right away. Prompt medical attention is critical for adults as well as for children even if you do not notice any signs or symptoms.

Directions:

Adults and children 12 years of age and older: Take 2 tablets every 4 to 6 hours as needed, do not exceed 8 tablets in 24 hours, or as directed by a doctor.

Children under 12 years: consult a doctor

INACTIVE INGREDIENT

Inactive Ingredients: corn starch, hydroxypropyl methylcelluslose*, maltodextrin*, polyethylen glycol*, microcrystalline cellulose, povidone, sodium starch glycolate, stearic acid

*contains one or more of these ingredients

PACKAGE LABEL

Extra Strength

PAIN RELIEVER

Acetaminophen

Pain Reliever / Fever Reducer

COMPARE TO THE ACTIVE INGREDIENTS IN

TYLENOL ® EXTRA STRENGTH*

6 TABLETS